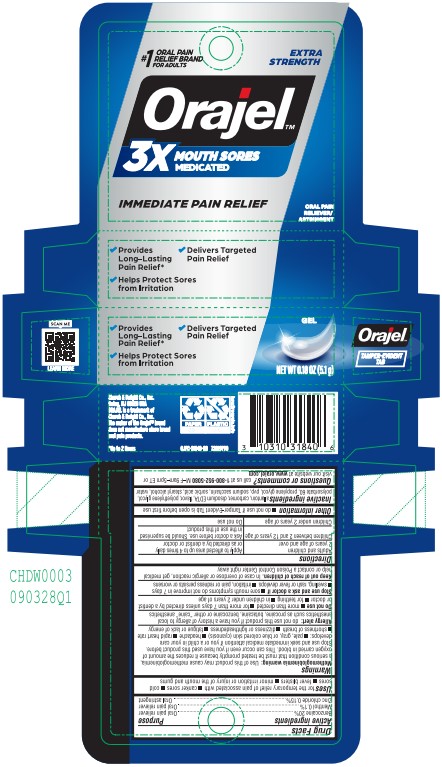 DRUG LABEL: Orajel 3X Medicated For All Mouth Sores
NDC: 10237-783 | Form: GEL
Manufacturer: Church & Dwight Co., Inc.
Category: otc | Type: HUMAN OTC DRUG LABEL
Date: 20251212

ACTIVE INGREDIENTS: BENZOCAINE 200 mg/1 g; MENTHOL 1 mg/1 g; ZINC CHLORIDE 1.5 mg/1 g
INACTIVE INGREDIENTS: CARBOMER 934; POVIDONE; SACCHARIN SODIUM; WATER; EDETATE DISODIUM; METHYL SALICYLATE; POLYETHYLENE GLYCOL, UNSPECIFIED; PROPYLENE GLYCOL; POLYSORBATE 60; SORBIC ACID; STEARYL ALCOHOL; ALLANTOIN

Orajel 3X Medicated For All Mouth Sores, Gel

ACTIVE INGREDIENT

Benzocaine 20%

Menthol 0.1%

Zinc Chloride 0.15%

PURPOSE

Oral pain reliever and Oral astringent

Use

for the temporary relief of pain associated with canker sores, cold sores, fever blisters, minor irritation or injury of the mouth and gums

WARNINGS

Methemoglobinemia warning: use of this product may cause methemoglobinemia, a serious condition that must be treated promptly because it reduces the amount of oxygen carried in blood. This can occur even if you have used this product before. Stop use and seek immediate medical attention if you or a child in your care develops: pale, gray, or blue colored skin (cyanosis), headache, rapid heart rate, shortness of breath, dizziness or lightheadedness, fatigue or lack of energy

Allergy alert: do not use this product if you have a history of allergy to local anesthetics such as procaine, butacaine, benzocaine or other "caine" anesthetics

DO NOT USE

- more than directed
- for more than 7 days unless directed by a dentist or doctor
- for teething
- in children under 2 years of age

Stop use and ask a doctor if

- sore mouth symptoms do not improve in 7 days
- swelling, rash or fever develops
- irritation, pain or redness persists or worsens

KEEP OUT OF REACH OF CHILDREN

In case of overdose or allergic reaction, get medical help or contact a Poison Control Center right away

Directions

Adults and children 2 years of age and over | Apply to affected area up to 4 times daily or as directed by a dentist or doctor
Children between 2 and 12 years of age | Ask a doctor before use. Should be supervised in the use of this product
Children under 2 years of age | Do not use

Other information

do not use if Tamper-Evident Tab is open before first use

INACTIVE INGREDIENT

allantoin, carbomer, disodium EDTA, flavor, polyethylene glycol, polysorbate 60, propylene glycol, pvp, sodium saccharin, sorbic acid, stearyl alcohol, water

Questions or comments?

call us at 1-800-952-5080 M-F 9am-5pm ET or visit our website at www.orajel.com

PACKAGE LABEL

#1 ORAL PAIN

RELIEF BRAND

FOR ADULTS

EXTRA STRENGTH

Orajel™

3X MOUTH SORES

MEDICATED

IMMEDIATE PAIN RELIEF

ORAL PAIN

RELIEVER/

ASTRINGENT

Provides

Long-Lasting

Pain Relief*

Helps Protect Sores

from Irritation

Delivers Targeted

Pain Relief

GEL

NET WT

0.18 OZ (5.1 g)